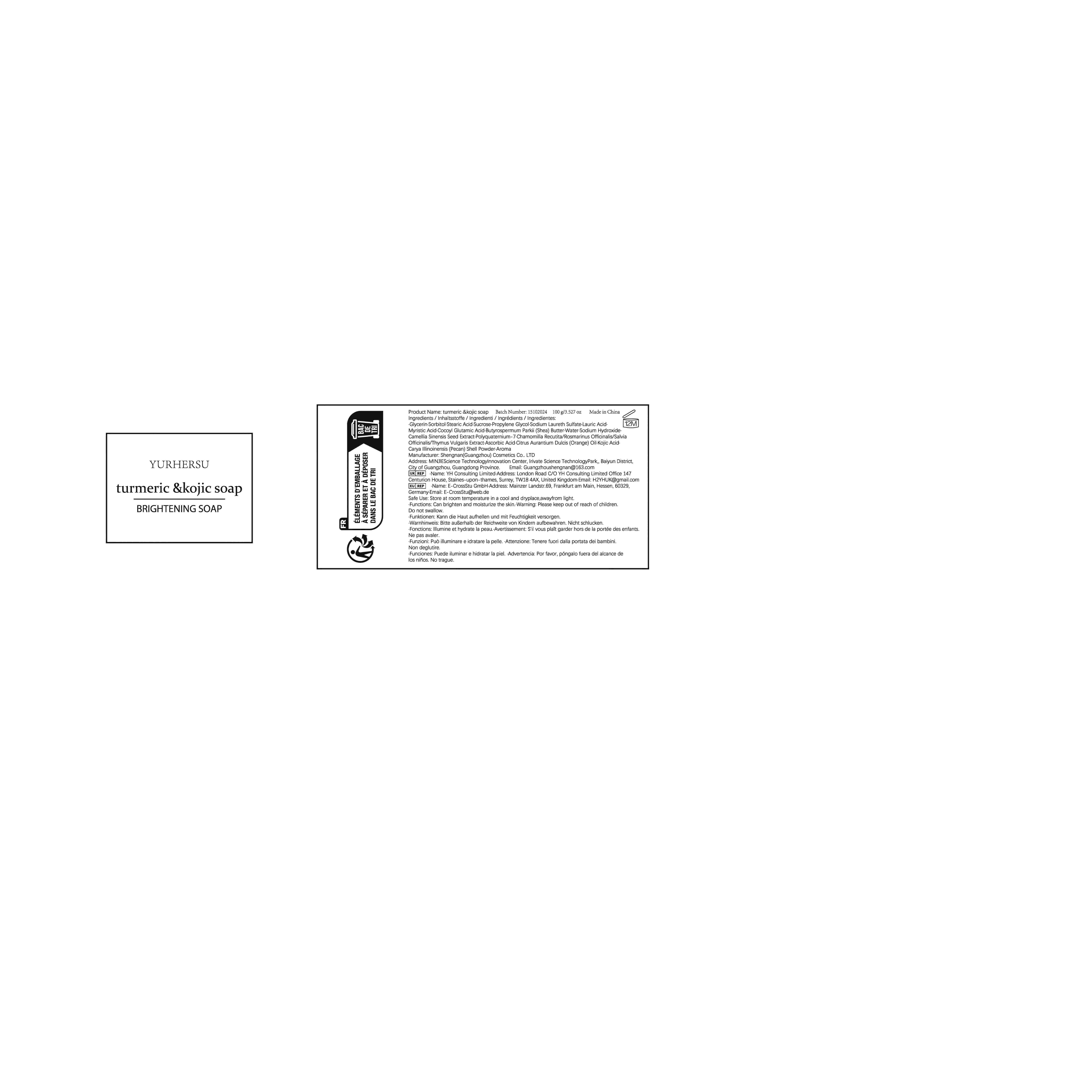 DRUG LABEL: TurmericKojicSoap
NDC: 84019-017 | Form: SOAP
Manufacturer: Shengnan (Guangzhou) Cosmetics Co., Ltd
Category: otc | Type: HUMAN OTC DRUG LABEL
Date: 20241219

ACTIVE INGREDIENTS: KOJIC ACID 100 mg/1 g
INACTIVE INGREDIENTS: STEARIC ACID; SORBITOL; GLYCERIN; SODIUM LAURETH SULFATE; LAURIC ACID; SUCROSE

WARNINGS

Please keep out of reach of children.Do not swa ow.

PURPOSE

BRIGHTENING

STOP USE

Discontinueuse if signs of irritation or rash occur

ACTIVE INGREDIENT

Kojic Acid

WHEN USING

Please clean your hands before use to ensure the best results fromthe product.

INACTIVE INGREDIENT

GLYCERIN
SORBITOL
STEARIC ACID
SUCROSE
PROPYLENE GLYCOL
SODIUM LAURETH SULFATE
LAURIC ACID
MYRISTIC ACID
COCOYL GLUTAMIC ACID
BUTYROSPERMUM PARKII (SHEA BUTTER)
WATER
SODIUM HYDROXIDE
CAMELLIA SINENSIS SEED EXTRACT
POLYQUATERNIUM-7
ROSMARINUS OFFICINALIS
ASCORBIC ACID
CITRUS AURANTIUM DULCIS (ORANGE) OIL
CARYA ILLINOENSIS (PECAN) SHELL POWDER
AROMA

DOSAGE AND ADMINISTRATION

Apply 1 times a day

INDICATIONS AND USAGE

1.Moisturizing the skin: Wash the face with warm water and wet the hands with warm water.2.Produce foam: wet the soap and rub it with hand or foam net to produce rich foam.3.Clean skin: Apply foam on the skin to clean in circles, and foam can take away dirt. After friction, stay on the skin for about 30 seconds to make the essence of the product penetrate into the bottom layer of the skin.4.Rinse clean: rinse the foam with warm water, and be careful not to let the soap liquid enter the eyes.